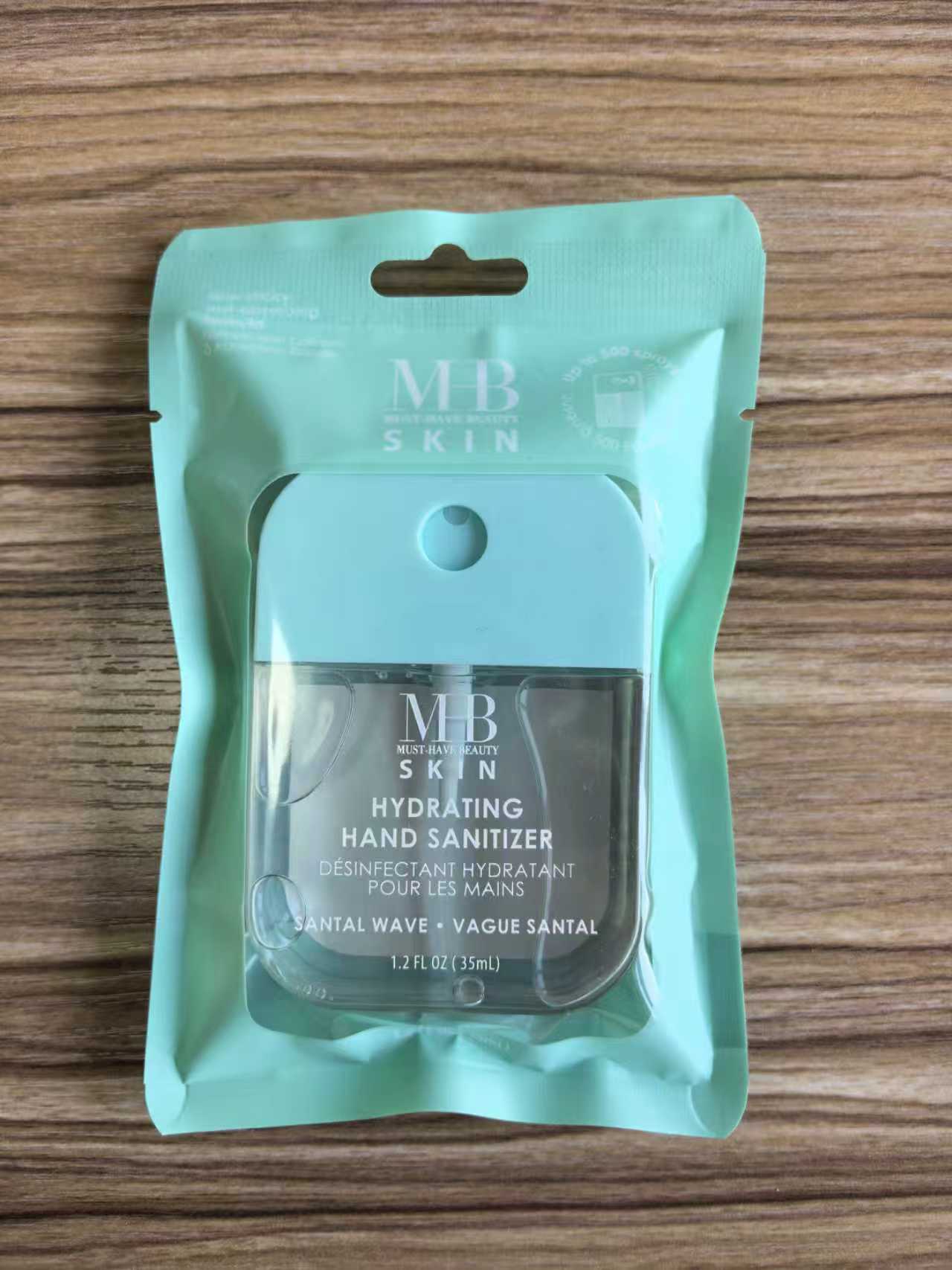 DRUG LABEL: MHB SKIN HYDRATING HAND SANITIZER SANTAL WAVE 35ml
NDC: 85537-111 | Form: SPRAY
Manufacturer: PT SUPER HOME PRODUCT INDONESIA
Category: otc | Type: HUMAN OTC DRUG LABEL
Date: 20260114

ACTIVE INGREDIENTS: ALCOHOL 70 mL/100 mL
INACTIVE INGREDIENTS: ALPHA-TOCOPHEROL ACETATE; GLYCERIN; AMINOMETHYLPROPANOL; AQUA; CI 42090; ALOE BARBADENSIS LEAF JUICE; CARBOMER; FRAGRANCE 13576

MHB SKIN HYDRATING HAND SANITIZER SANTAL WAVE 35ml

Directions:

Spray onto hands and rub together until dry. Recommended for repeat use.Children under 6 years of age should be supervised when using this product.

Inactive Ingredients：

Water (Aqua), Glycerin, Fragrance, Aloe Barbadensis Leaf Juice, Carbomer, Aminomethyl Propanol, Tocopheryl Acetate (Vitamin E). CI42090

Warnings：

For external use only, Flammable, keep away from fire or flame.

When using this product:

In case of contact with eyes, rinse eyes thoroughly with water. Avoid contact with broken skin

Stop use and ask a doctor if:

lrritation and redness occurs

Keep out of reach of children:

If swallowed, get medical help or contact a Poison Control Center.

Active Ingredients:

Ethyl Alcohol 70% v/v Purpose: Antimicrobial

Use:

Hand sanitizer helps reduce bacteria and the spread of germs.